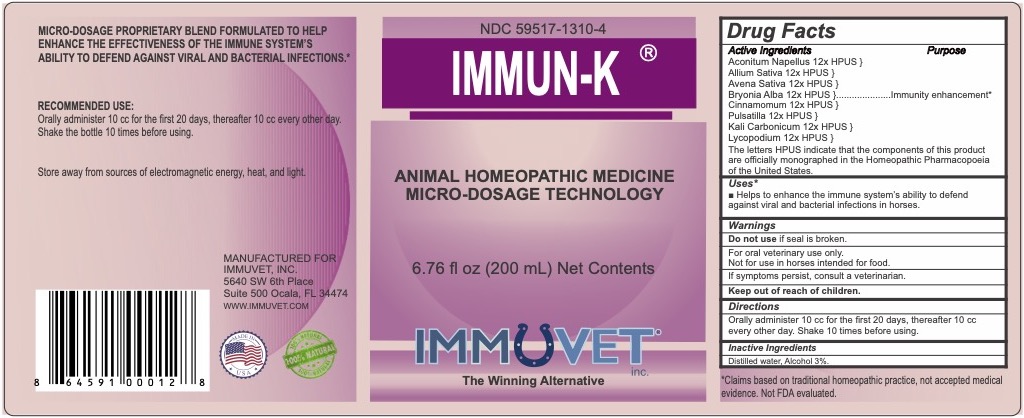 DRUG LABEL: IMMUN-K
NDC: 59517-1310 | Form: LIQUID
Manufacturer: Immuvet, Inc.
Category: homeopathic | Type: OTC ANIMAL DRUG LABEL
Date: 20251104

ACTIVE INGREDIENTS: ACONITUM NAPELLUS 12 [hp_X]/1 mL; GARLIC 12 [hp_X]/1 mL; AVENA SATIVA FLOWERING TOP 15 [hp_X]/1 mL; BRYONIA ALBA ROOT 12 [hp_X]/1 mL; ANEMONE PULSATILLA 12 [hp_X]/1 mL; POTASSIUM CARBONATE 12 [hp_X]/1 mL; LYCOPODIUM CLAVATUM SPORE 12 [hp_X]/1 mL; CINNAMON 12 [hp_X]/1 mL
INACTIVE INGREDIENTS: ALCOHOL; WATER

IMMUN-K

PURPOSE

Immunity enhancement in horses.

DIRECTIONS

Orally administer 10 cc for the first 20 days, thereafter 10 cc every other day. Shake 10 times before using.

ACTIVE INGREDIENTS

Aconitum Napellus 12x HPUS
Allium Sativa 12x HPUS
Avena Sativa 12x HPUS
Bryonia Alba 12x HPUS
Cinnamomum 12x HPUS
Pulsatilla 12x HPUS
Kali Carbonicum 12x HPUS
Lycopodium 12x HPUS

INACTIVE INGREDIENTS

Distilled water, Alcohol 3%

WARNINGS

Do not use if seal is broken.
For Oral Veterinary Use Only.
Not for use in Horses intended for food.
If problems persist, contact a veterinarian.
Keep out of reach of children.

OTHER INFORMATION

Claims based on traditional homeopathic practice, not accepted medical evidence. Not FDA evaluated.